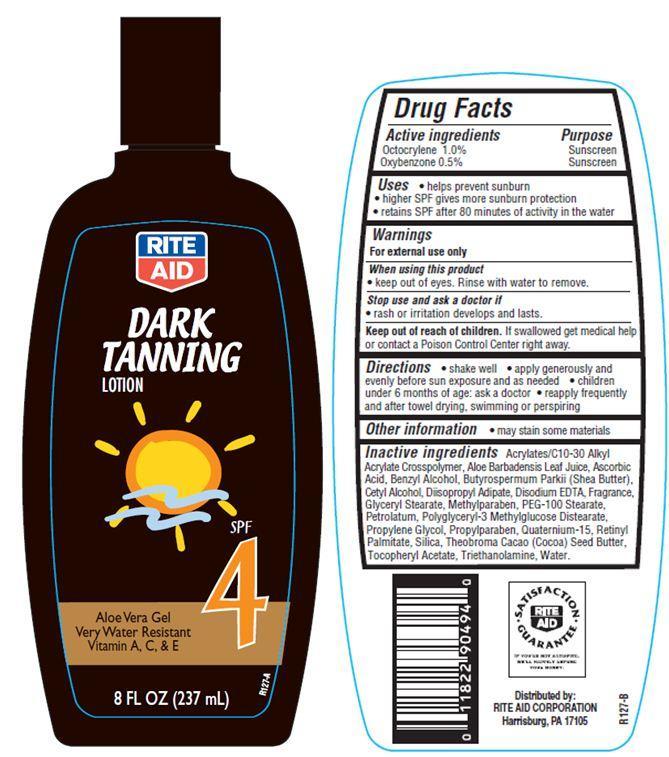 DRUG LABEL: Rite Aid Dark Tanning
NDC: 11822-9006 | Form: LOTION
Manufacturer: RITE AID CORPORATION
Category: otc | Type: HUMAN OTC DRUG LABEL
Date: 20121121

ACTIVE INGREDIENTS: OCTOCRYLENE 1 g/100 g; OXYBENZONE 0.5 g/100 g
INACTIVE INGREDIENTS: WATER; PETROLATUM; DIISOPROPYL ADIPATE; PROPYLENE GLYCOL; SILICON DIOXIDE; CETYL ALCOHOL; GLYCERYL MONOSTEARATE; TROLAMINE; PEG-100 STEARATE; .ALPHA.-TOCOPHEROL ACETATE; EDETATE DISODIUM; BENZYL ALCOHOL; COCOA BUTTER; SHEA BUTTER; ALOE VERA LEAF; OCTYLDODECANOL; VITAMIN A PALMITATE; ASCORBIC ACID; METHYLPARABEN; PROPYLPARABEN; QUATERNIUM-15

Drug Facts

Active ingredients

Octocrylene 1.0%
Oxybenzone 0.5 %

Purpose

Sunscreen

Uses

- helps prevent sunburn
- higher SPF gives more sunburn protection
- retains SPF after 80 minutes of activity in the water

Warnings

For external use only

When using this product

- keep out of eyes. Rinse with water to remove

Stop use and ask a doctor if

- rash or irritation develops and lasts.

Keep Out of the reach of children.

If swallowed get medical help or contact a Poison Control Center right away.

Directions

- shake well
- apply generously and evenly before sun exposure and as needed
- children under 6 months of age:ask a doctor
- reapply frequently and after towel drying, swimming or perspiring.

Other Information

- may stain some materials

Inactive ingredients

Water, Petrolatum, Diisopropyl Adipate, Propylene Glycol, Polyglyceryl-3 Methylglucose Distearate, Cetyl Alcohol, Glyceryl Stearate, PEG-100 Stearate, Acrylates/C10-30 Alkyl Acrylate Crosspolymer, Triethanolamine, Benzyl Alcohol, Theobroma Cacao (Cocoa) Seed Butter, Butyrospermum Parkii (Shea) Butter, Disodium EDTA, Aloe Barbadensis Leaf Juice Powder, Octyldodecanol, Retinyl Palmitate, Silica, Tocopheryl Acetate, Ascorbic Acid, Sodium Propoxyhydroxypropyl Thiosulfate Silica, Methylparaben, Propylparaben, Quaternium-15, Fragrance.

Principal Display Panel

RITE
AID
DARK
TANNING
LOTION
SPF
4
Aloe vera Gel
Very Water Resistant
Vitamins A, C and E
8 FL OZ (237 mL)